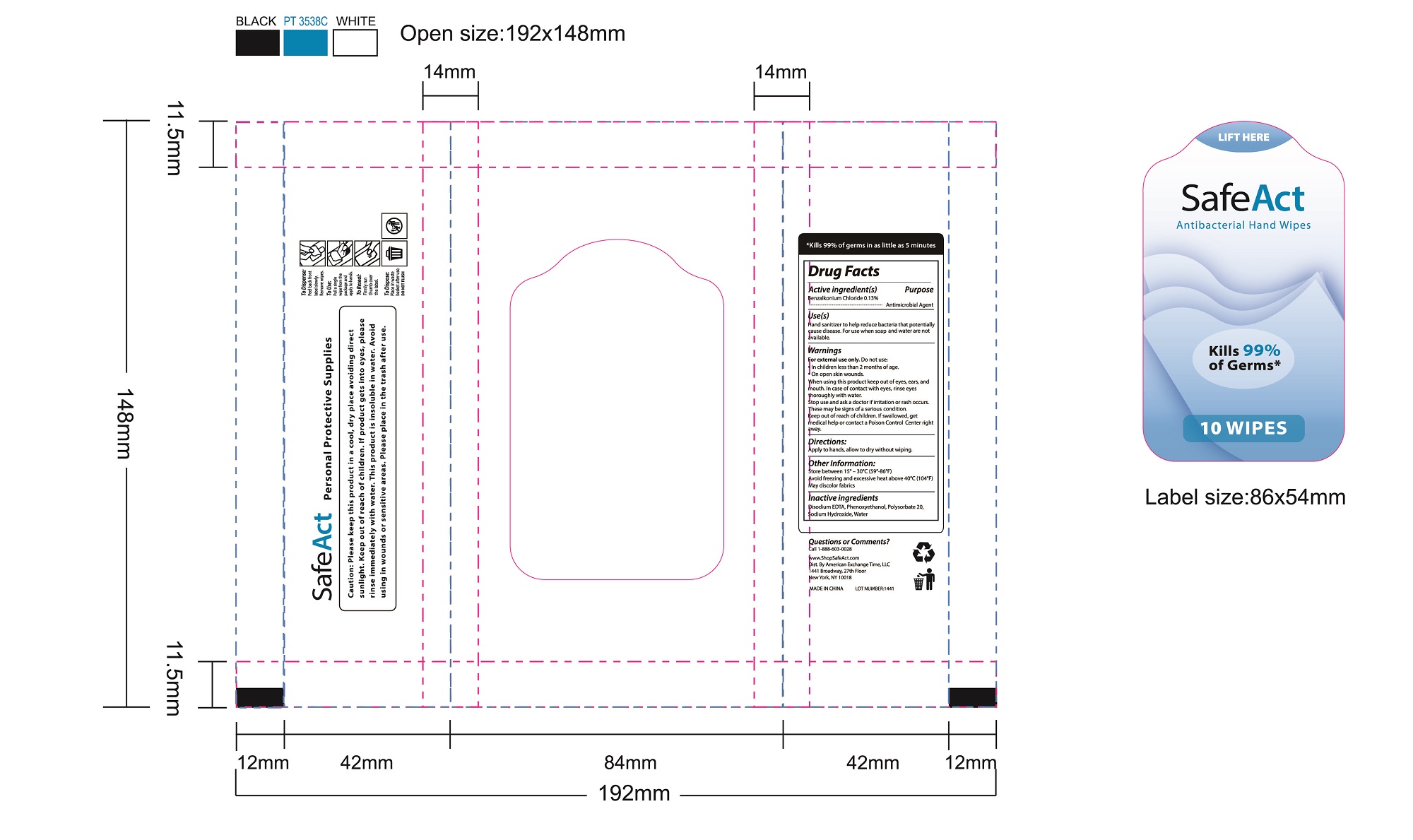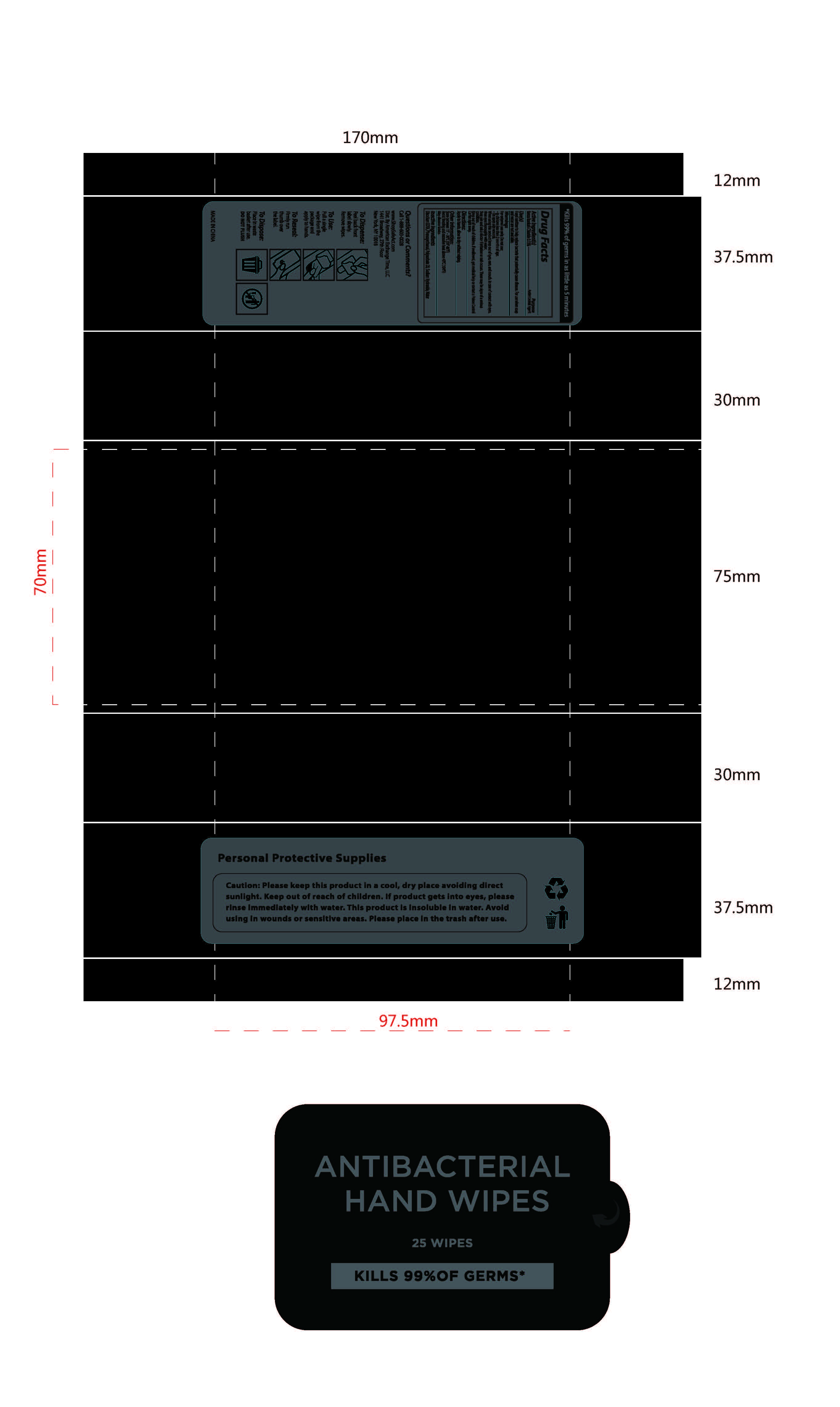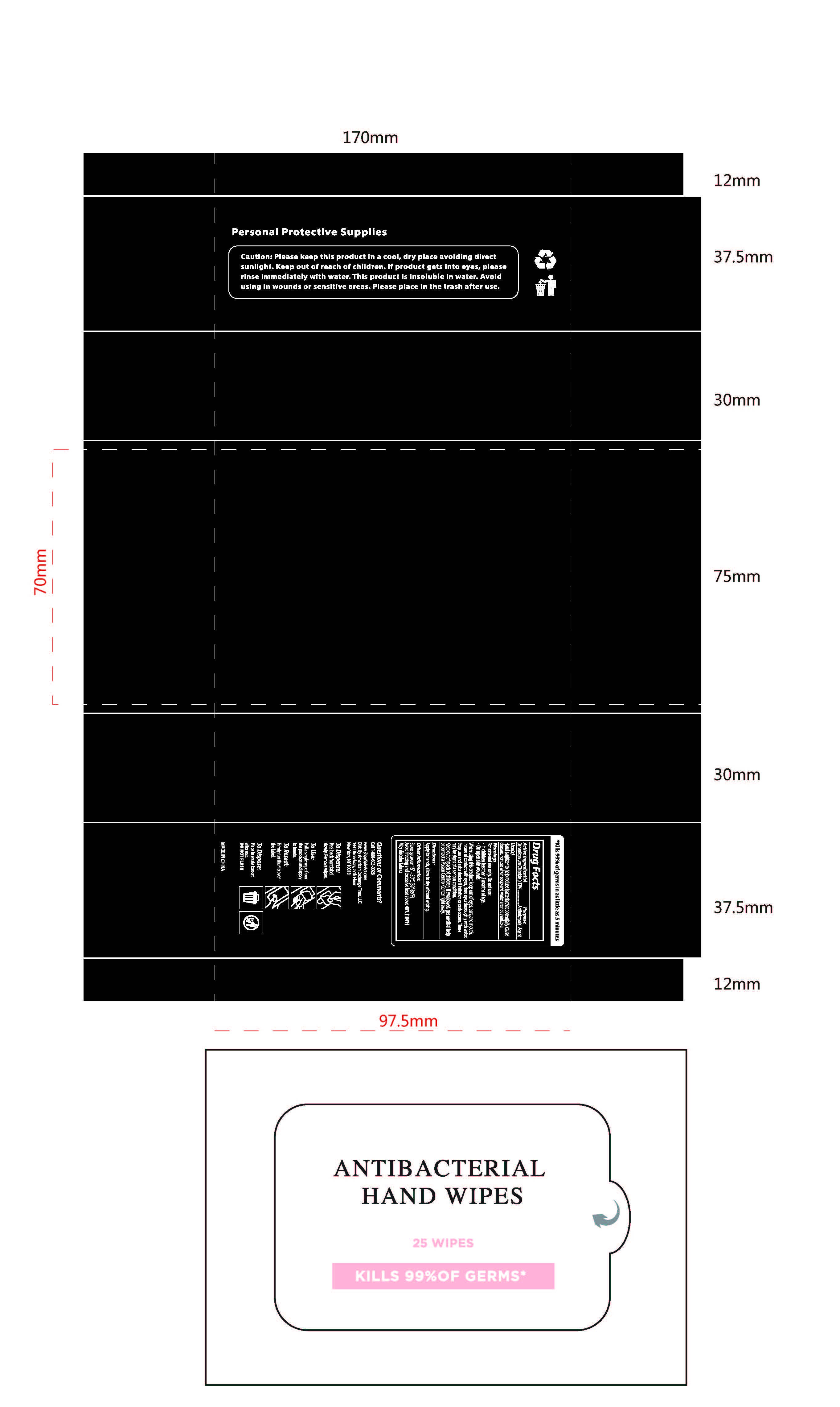 DRUG LABEL: Safeact Claening Wipes
NDC: 78870-902 | Form: CLOTH
Manufacturer: AMERICAN EXCHANGE TIME LLC
Category: otc | Type: HUMAN OTC DRUG LABEL
Date: 20200824

ACTIVE INGREDIENTS: BENZALKONIUM CHLORIDE 0.13 g/100 g
INACTIVE INGREDIENTS: PHENOXYETHANOL; EDETATE DISODIUM ANHYDROUS; WATER; SODIUM HYDROXIDE; POLYSORBATE 20

78870-902 Safeact cleaning wipes 0.13% Benzalkonium Chloride

Active Ingredient

Benzalkonium Chloride 0.13 %

Purpose

Antimicrobial Agent

USE

Hand sanitizer to help reduce bacteria that potentially
cause disease. For use when soap and water are not
available.

Warning

For external use only. Do not use:
In children less than 2 months of age.
On open skin wounds.
When using this product keep out of eyes, ears, and
mouth, In case of contact with eyes, rinse eyes
thoroughly with water.
Stop use and ask a doctor if rritation or rash occurs.
These may be signs of a serious condition.

Keep out of reach of children. If swallowed, get
medical help or contact a Poison Control Center right
away.

Directions

Apply to hands, allow to dry without wiping.